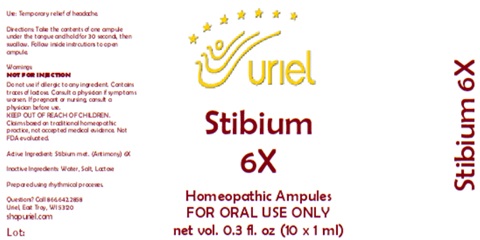 DRUG LABEL: Stibium 6
NDC: 48951-8213 | Form: LIQUID
Manufacturer: Uriel Pharmacy Inc.
Category: homeopathic | Type: HUMAN OTC DRUG LABEL
Date: 20260225

ACTIVE INGREDIENTS: ANTIMONY 6 [hp_X]/1 mL
INACTIVE INGREDIENTS: WATER; SODIUM CHLORIDE; LACTOSE

Stibium 6

PURPOSE

Use: Temporary relief of headache.

INDICATIONS AND USAGE

FOR ORAL USE ONLY

DOSAGE AND ADMINISTRATION

Directions: Take the contents of one ampule under the tongue and hold for 30 seconds, then swallow. Follow inside instrcutions to open ampule.

Warnings:
NOT FOR INJECTION
Do not use if allergic to any ingredient. Contains traces of lactose. Consult a physician if symptoms worsen. If pregnant or nursing, consult a physician before use.
Claims based on traditional homeopathic practice, not accepted medical evidence. Not FDA evaluated.

KEEP OUT OF REACH OF CHILDREN.

Active Ingredient: Stibium met. (Antimony) 6X

Inactive Ingredients: Water, Salt, Lactose

Prepared using rhythmical processes.

Questions? Call 866.642.2858
Uriel, East Troy, WI 53120
shopuriel.com Lot: